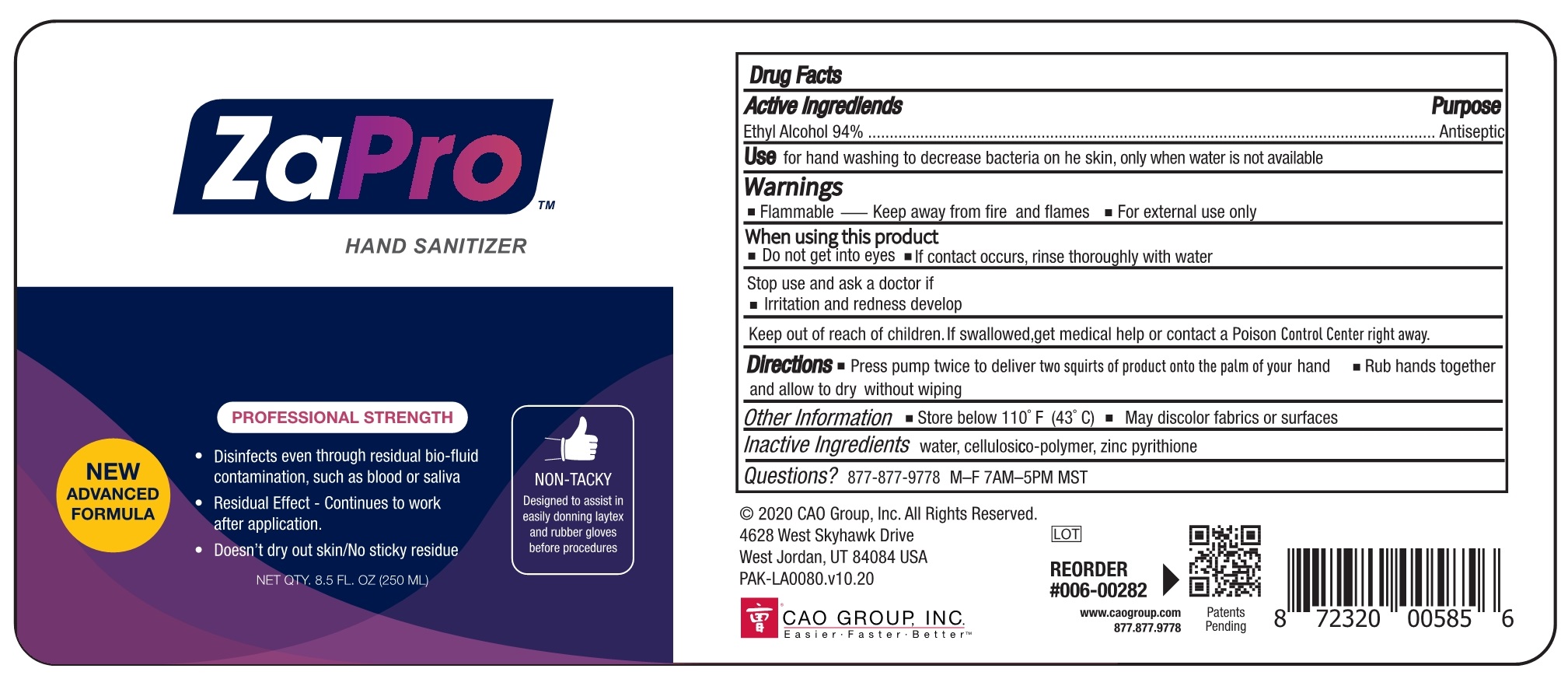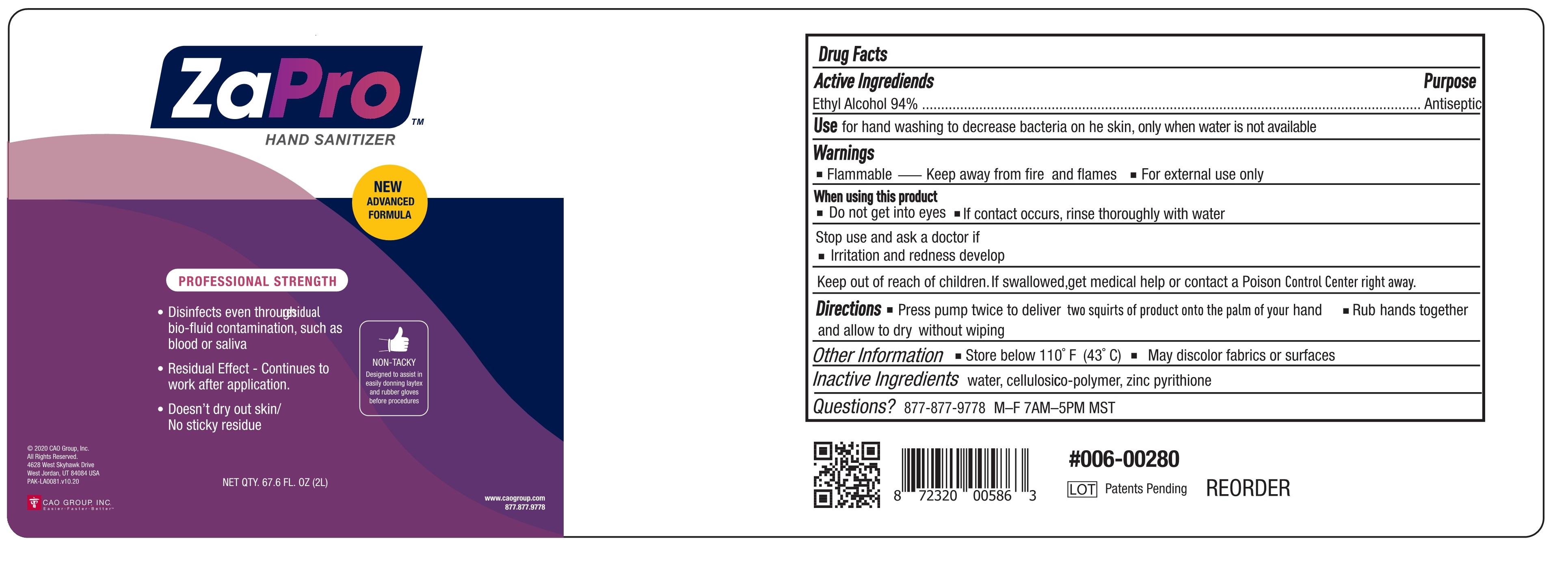 DRUG LABEL: ZAPRO HAND SANITIZER
NDC: 75209-011 | Form: GEL
Manufacturer: GUANGDONG MINGLIU TECHNOLOGY DAIL-USE CHEMICAL CO., LTD.
Category: otc | Type: HUMAN OTC DRUG LABEL
Date: 20201226

ACTIVE INGREDIENTS: ALCOHOL 94 mL/100 mL
INACTIVE INGREDIENTS: PYRITHIONE ZINC; WATER; POWDERED CELLULOSE

75209-011
ZAPRO HAND SANITIZER

Active Ingredient(s)

Ethyl Alcohol 94%

Purpose

Antiseptic

Use

for hand washing to decrease bacteria on he skin， only when water is not ava able

Warnings

Flammable—Keep away from fire and flames
For external use only

Do not use

Do not get into eyes
lf contact occurs， rinse thoroughly with water

When using this product

Do not get into eyes
lf contact occurs， rinse thoroughly with water

Stop use and ask a doctor if
Irritation and redness develop

Keep out of reach of children.If swallowed， get medical help or contact a Poison Control Center right away.

Stop use and ask a doctor if
Irritation and redness develop

Keep out of reach of children.If swallowed， get medical help or contact a Poison Control Center right away.

Directions

Press pump twice to dever two s quits of product on to the pam of your hand
Rub hands together and allow to dry without wiping

Other information

May discolor fabrics or surfaces
Store below 110°F(43°C)

Inactive ingredients

water, cellulosico-polymer, zinc pyrithione

Package Label - Principal Display Panel

75209-011-01 250ml

75209-011-02 2000ml